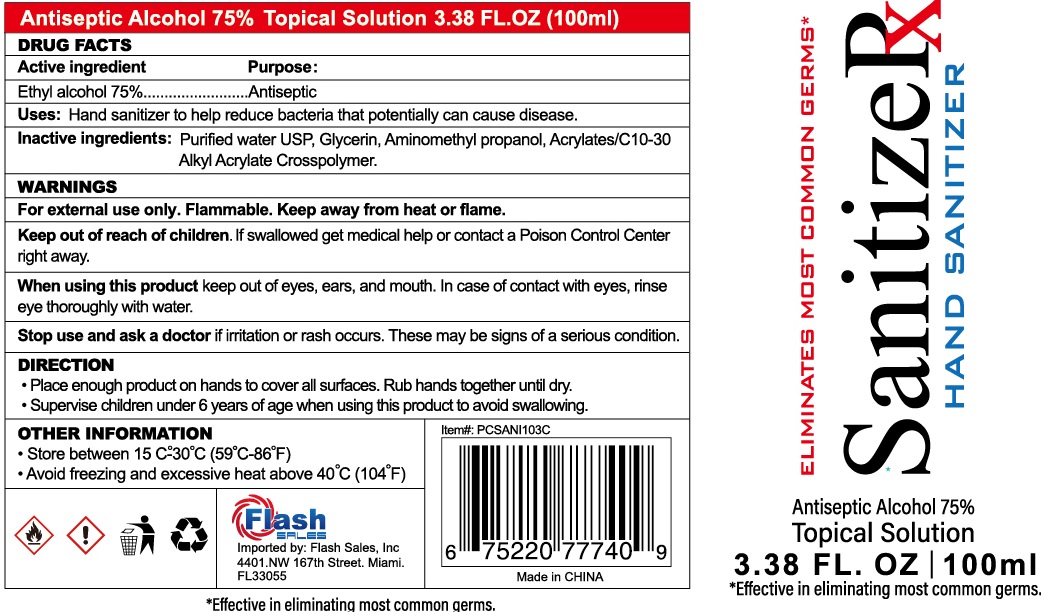 DRUG LABEL: Sanitizerx Hand Sanitizer
NDC: 56136-027 | Form: SOLUTION
Manufacturer: Ganzhou Olivee Cosmetic Co., Ltd.
Category: otc | Type: HUMAN OTC DRUG LABEL
Date: 20200511

ACTIVE INGREDIENTS: ALCOHOL 75 mL/100 mL
INACTIVE INGREDIENTS: WATER; CARBOMER INTERPOLYMER TYPE A (ALLYL SUCROSE CROSSLINKED); AMINOMETHYLPROPANOL; CARBOMER COPOLYMER TYPE A; .ALPHA.-TOCOPHEROL ACETATE, DL-; GLYCERIN

HAND SANITIZER

Active ingredient

Ethyl Alcohol 75%

Purpose

Antiseptic

Use

Hand sanitizer to help reduce bacteria that potential can cause disease.

Warnings

For external use only.

Flammable. Keep product away from heat or flame.

When using this product keep out of eyes, ears, and mouth. In case of contact with eyes, rinse eyes thoroughly with water.

Stop use and ask a doctor if irritation or rash occurs. These may be signs of serious condition.

Other Information

- Store between 15-30℃ (59-86℉)
- Avoid freezing and excessive heat above 40℃ (104℉)

Keep out of reach of children.

If swallowed, get medical help or contact a Poison Control Center right away.

Directions

- Place enough product on hands to cover all surfaces. Rub hands together until dry.
- Supervise children under 6 years of age when using this product to avoid swallowing.

Inactive ingredients

Alcohol Denat, Water (Aqua), Glycerin, Acrylates/C10-30 Alkyl Acrylate Crosspolymer, Aminomethyl Propanol